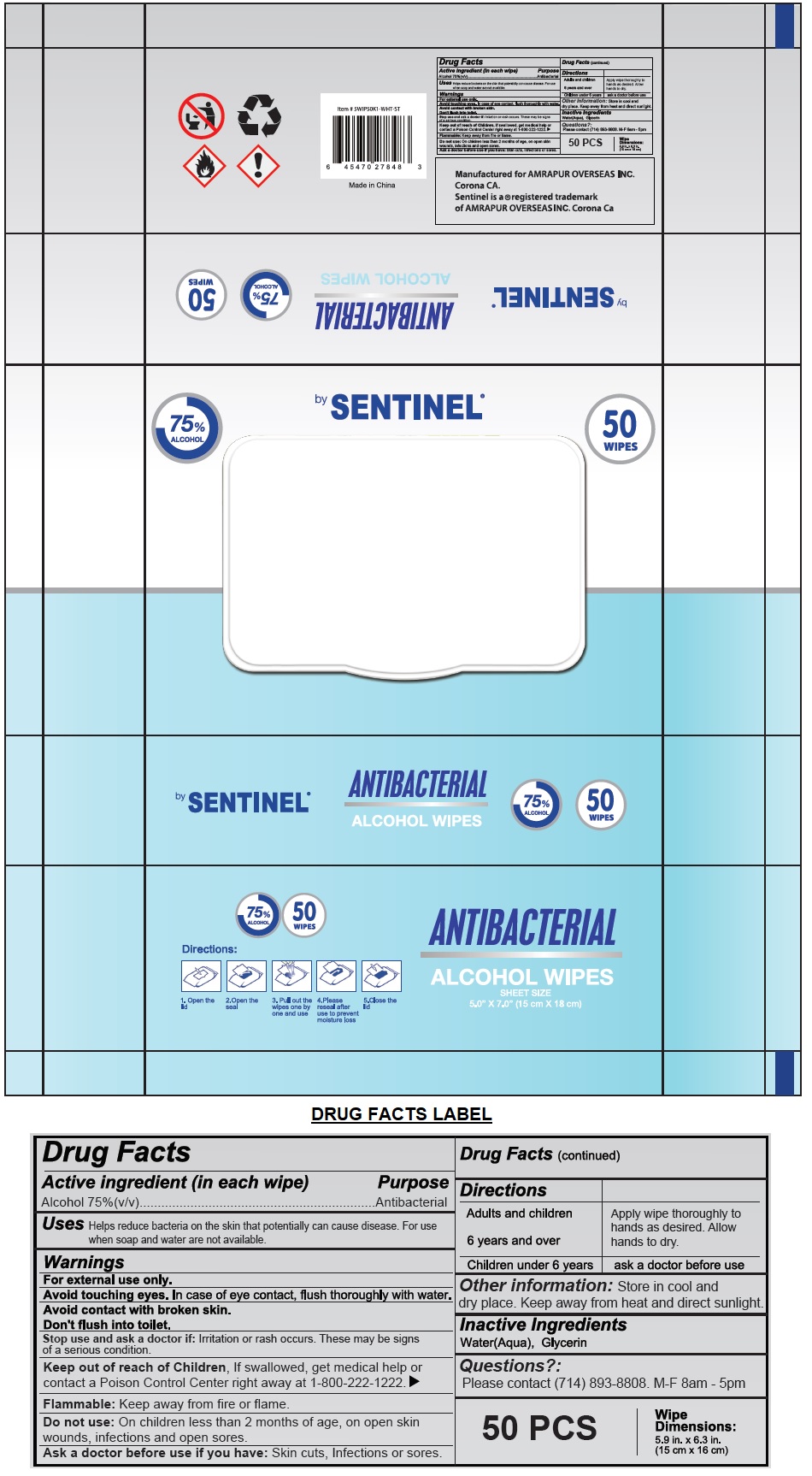 DRUG LABEL: Sentinel ANTIBACTERIAL ALCOHOL WIPES
NDC: 80147-075 | Form: CLOTH
Manufacturer: Amrapur Overseas Incorporated
Category: otc | Type: HUMAN OTC DRUG LABEL
Date: 20201116

ACTIVE INGREDIENTS: ALCOHOL 75 mL/100 mL
INACTIVE INGREDIENTS: WATER; GLYCERIN

by SENTINEL® ANTIBACTERIAL ALCOHOL WIPES

Active ingredient (in each wipe)

Alcohol 75%(v/v)

Purpose

Antibacterial

Uses

Helps reduce bacteria on the skin that potentially can cause disease. For use when soap and water are not available.

Warnings

For external use only.

Avoid touching eyes. In case of eye contact, flush thoroughly with water.

Avoid contact with broken skin.

Don't flush into toilet.

Stop use and ask a doctor if: Irritation or rash occurs. These may be signs of a serious condition.

Flammable: Keep away from fire or flame.

Do not use: On children less than 2 months of age, on open skin wounds, infections and open sores.

Ask a doctor before use if you have: Skin cuts, Infections or sores.

Keep out of reach of Children, If swallowed, get medical help or contact a Poison Control Center right away at 1-800-222-1222.

Directions

Adults and children 6 years and over | Apply wipe thoroughly to hands as desired. Allow hands to dry.
Children under 6 years | ask a doctor before use

Other information:

Store in cool and dry place. Keep away from heat and direct sunlight.

Inactive Ingredients

Water(Aqua), Glycerin

Questions?:

Please contact (714) 893-8808. M-F 8am - 5pm

Wipe Dimensions:

5.9 in. x 6.3 in.

(15 cm x 16 cm)

75% ALCOHOL

Directions:

1. Open the lid

2. Open the seal

3. Pull out the wipes one by one and use

4. Please reseal after use to prevent moisture loss

5. Close the lid

Manufactured for AMRAPUR OVERSEAS INC.

Corona CA.

Sentinel is a ® registered trademark of AMRAPUR OVERSEAS INC. Corona Ca

Made in China